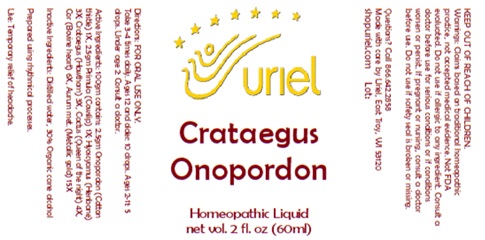 DRUG LABEL: Crataegus Onopordon
NDC: 48951-3278 | Form: LIQUID
Manufacturer: Uriel Pharmacy, Inc
Category: homeopathic | Type: HUMAN OTC DRUG LABEL
Date: 20250103

ACTIVE INGREDIENTS: GOLD 15 [hp_X]/1 mL; BEEF HEART 6 [hp_X]/1 mL; ONOPORDUM ACANTHIUM FLOWER 1 [hp_X]/1 mL; PRIMULA VERIS FLOWER 1 [hp_X]/1 mL; HYOSCYAMUS NIGER LEAF 3 [hp_X]/1 mL; HAWTHORN LEAF WITH FLOWER 3 [hp_X]/1 mL; SELENICEREUS GRANDIFLORUS STEM 4 [hp_X]/1 mL
INACTIVE INGREDIENTS: WATER; ALCOHOL

Crataegus Onopordon

INDICATIONS AND USAGE

Directions: FOR ORAL USE ONLY.

DOSAGE AND ADMINISTRATION

Take 3-4 times daily. Ages 12 and older: 10 drops. Ages 2-11: 5 drops. Under age 2: Consult a doctor.

ACTIVE INGREDIENT

Active Ingredients: 100gm contains: 2.5gm Onopordon (Cotton thistle) 1X, 2.5gm Primula (Cowslip) 1X; Hyoscyamus (Henbane) 3X; Crataegus (Hawthorn) 3X, Cactus (Queen of the night) 4X, Cor (Bovine heart) 6X, Aurum met. (Metallic gold) 15X

Inactive Ingredients: Distilled water, 30% Organic cane alcohol

Prepared using rhythmical processes.

PURPOSE

Use: Temporary relief of headache.

KEEP OUT OF REACH OF CHILDREN.

WARNINGS

Warnings: Claims based on traditional homeopathic practice, not accepted medical evidence. Not FDA evaluated. Do not use if allergic to any ingredient. Consult a doctor before use for serious conditions or if conditions worsen or persist. If pregnant or nursing, consult a doctor before use. Do not use if safety seal is broken or missing.

Questions? Call 866.642.2858
Made with care by Uriel, East Troy, WI 53120
shopuriel.com Lot: